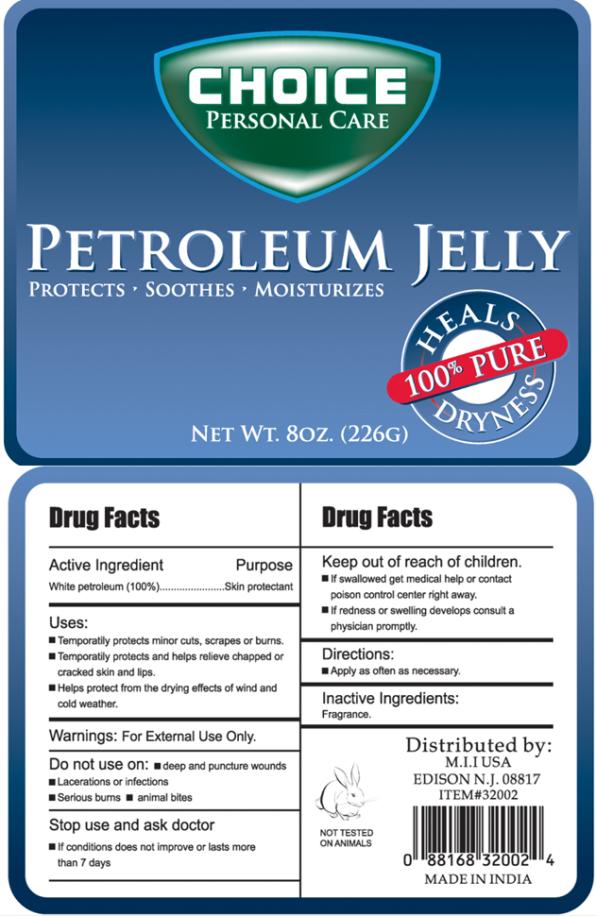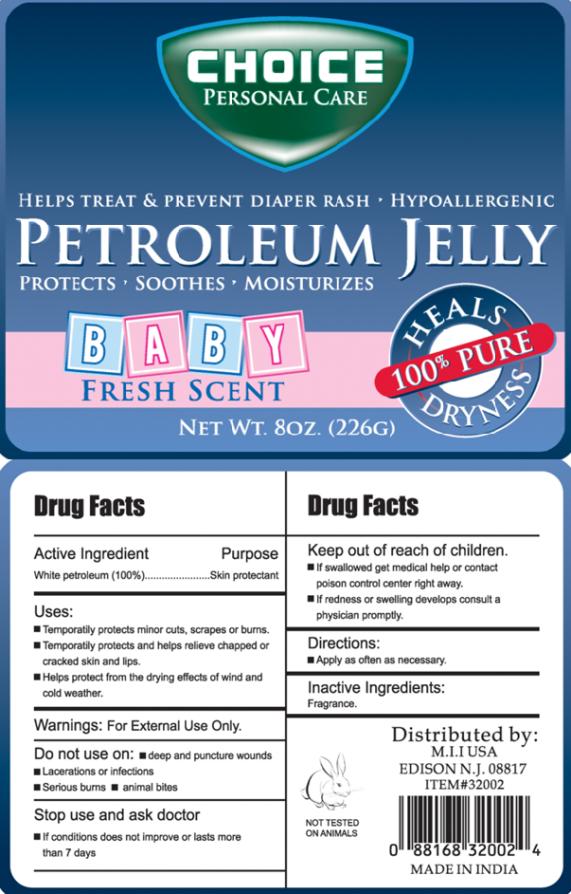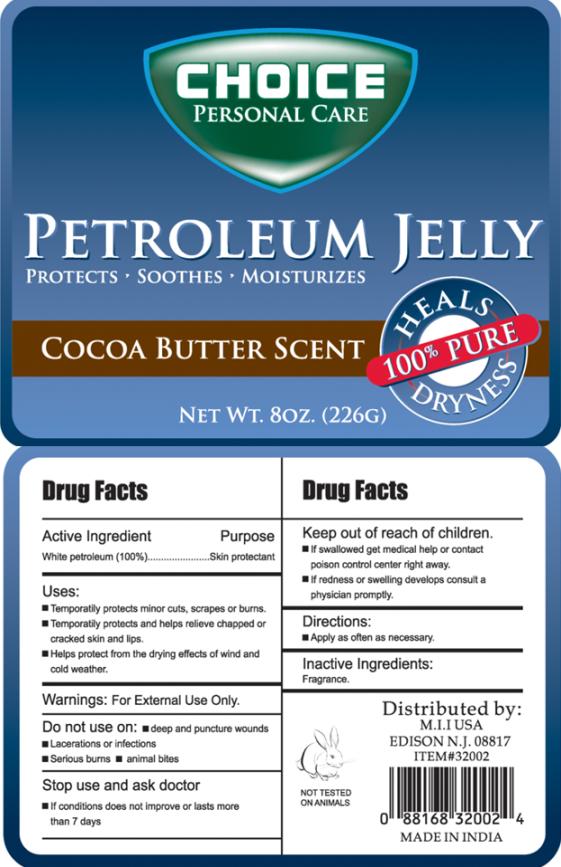 DRUG LABEL: Choice Personal Care Petroleum
NDC: 51628-3535 | Form: JELLY
Manufacturer: My Import Inc
Category: otc | Type: HUMAN OTC DRUG LABEL
Date: 20101104

ACTIVE INGREDIENTS: PETROLATUM 1 g/1 g

Petroleum Jelly

Drug Facts

Active Ingredient

White petroleum (100%)

Purpose

Skin protectant

Uses:

- Temporarily protects minor cuts, scrapes, or burns.
- Temporarily protects and helps relieve chapped or cracked skin and lips.
- Helps protect from the drying effects of wind and cold weather.

Warnings:

For External Use Only.

Do not use on:

- deep and puncture wounds
- Lacerations or infections
- Serious burns
- animal bites

Stop use and ask doctor

- If conditions does not improve or lasts more than 7 days

Keep out of reach of children.

- If swallowed get medical help or contact poison control center right away.
- If redness or swelling develops consult a physician promptly.

Directions:

- Apply as often as necessary.

Inactive Ingredients:

Fragrance.

PRINCIPAL DISPLAY PANEL

CHOICE PERSONAL CARE
PETROLEUM JELLY
PROTECTS SOOTHES MOISTURIZES
NET WT. 8OZ. (226G)

PRINCIPAL DISPLAY PANEL

CHOICE PERSONAL CARE
HELPS TREAT & PREVENT DIAPER RASH HYPOALLERGENIC
PETROLEUM JELLY
BABY FRESH SCENT
NET WT. 8OZ. (226G)

PRINCIPAL DISPLAY PANEL

CHOICE PERSONAL CARE
PETROLEUM JELLY
PROTECTS SOOTHES MOISTURIZES
COCOA BUTTER SCENT
NET WT. 8OZ. (226G)